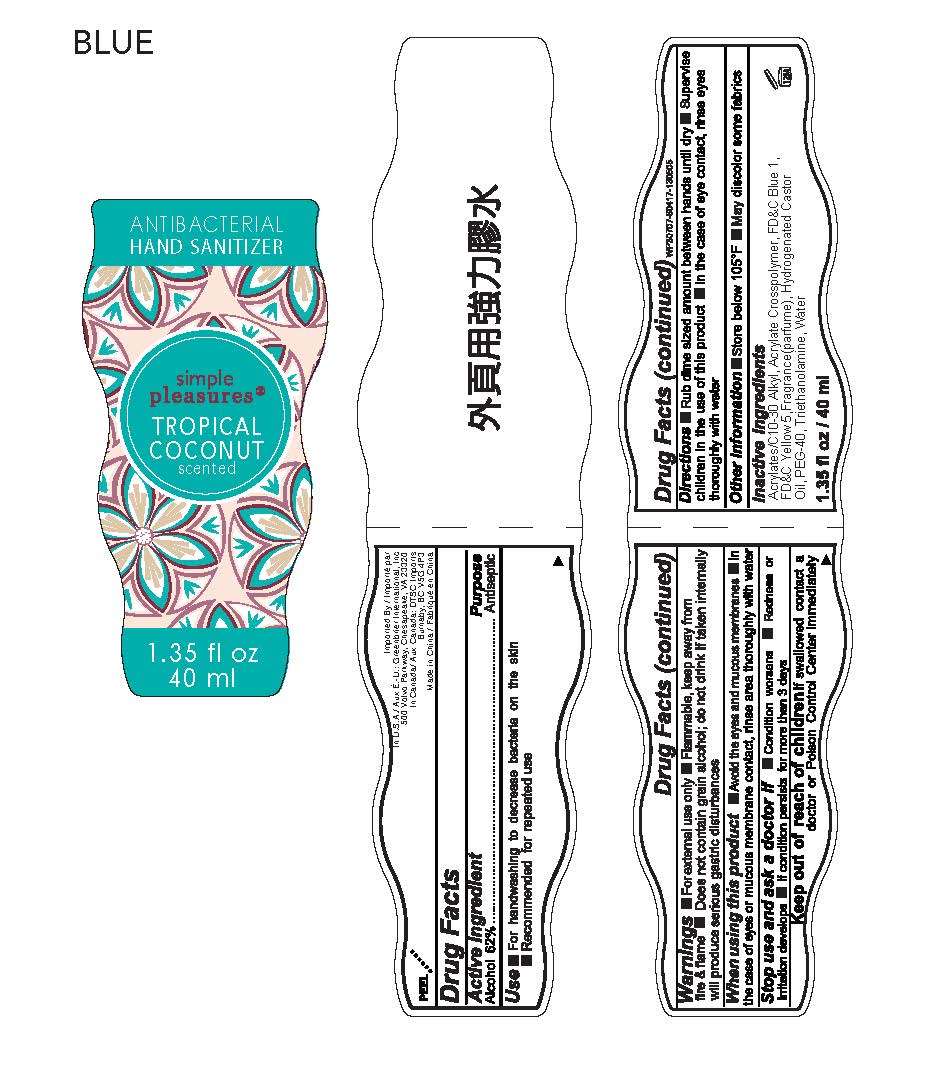 DRUG LABEL: simple pleasures
NDC: 33992-1419 | Form: LIQUID
Manufacturer: GREENBRIER INTERNATIONAL, INC.
Category: otc | Type: HUMAN OTC DRUG LABEL
Date: 20171206

ACTIVE INGREDIENTS: ALCOHOL 62 g/100 mL
INACTIVE INGREDIENTS: TROLAMINE; CARBOMER COPOLYMER TYPE A (ALLYL PENTAERYTHRITOL CROSSLINKED); FD&C BLUE NO. 1; WATER; FD&C YELLOW NO. 5; HYDROGENATED CASTOR OIL

Drug Facts

Active Ingredient

Alcohol 62%

Purpose

Antiseptic

Uses

■ For handwashing to decrease bacteria on the skin

■ Recommended for repeated use

Warnings

■ For external use only ■ Flammable, keep away from fire & flame ■ Does not contain grain alcohol;do not drink. If taken internally will produce serious gastric disturbances

When using this product

■ Avoid the eyes and mucous membranes ■ In the case of eyes or mucous membrane contact, rinse area thoroughly with water

Stop use and ask a doctor if

■ Condition worsens ■ Redness or irritation develops ■ If condition persists for more than 3 days

Keep out of reach of children

If swallowed contact a doctor or Poison Control Center immediately.

Directions

■ Rub dime sized amount between hands until dry ■ Supervise children in the use of this product ■ In the case of eye contact, rinse eyes thoroughly with water

Other information

■ Store below 105°F ■ May discolor some fabrics

Inactive Ingredients

Acrylates/C10-30 Alkyl Acrylate Crosspolymer, FD&C Blue 1, FD&C Yellow 5, Fragrance (parfume), Hydrogenated Castor Oil, PEG-40, Triethanolamine, Water